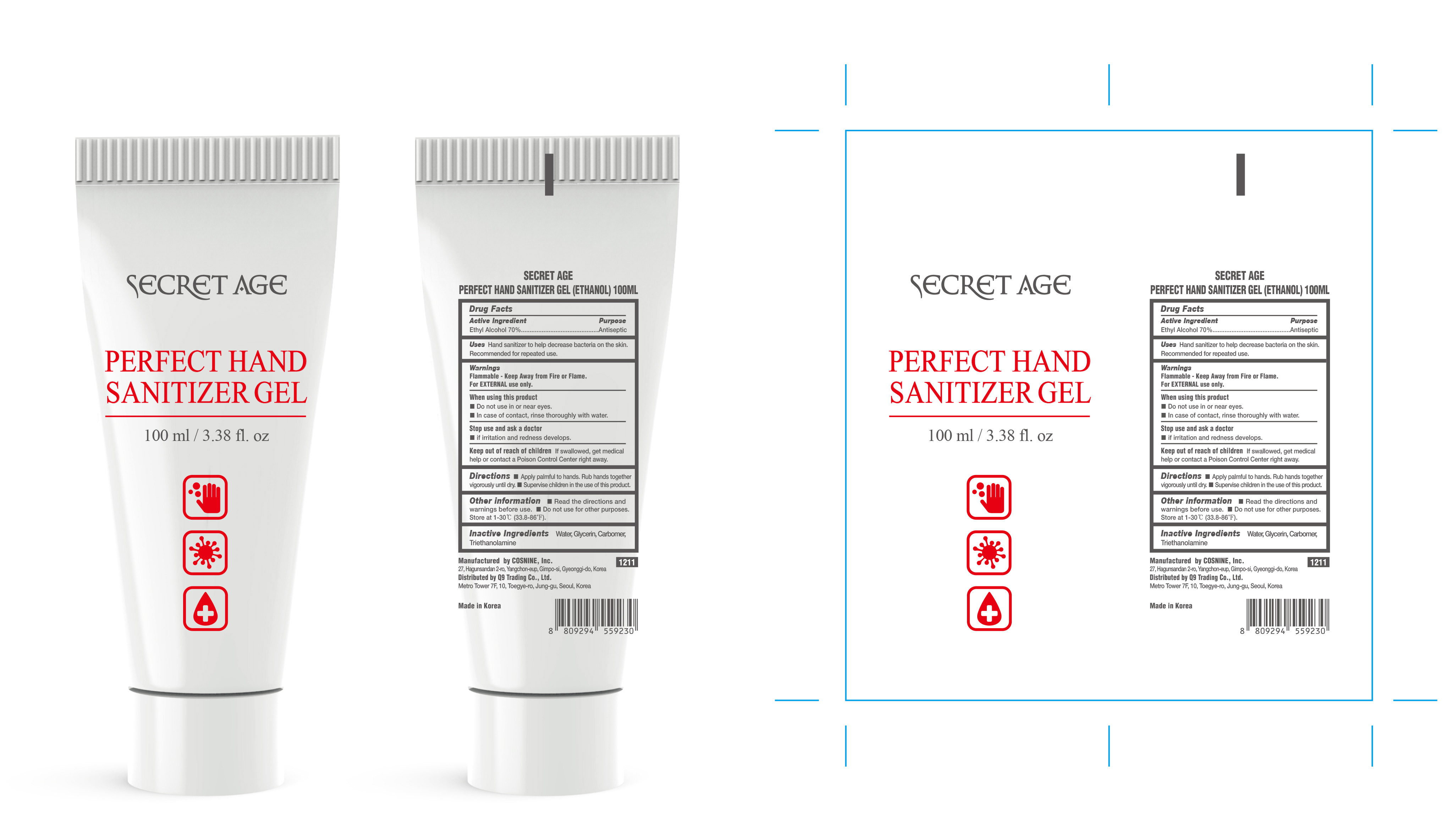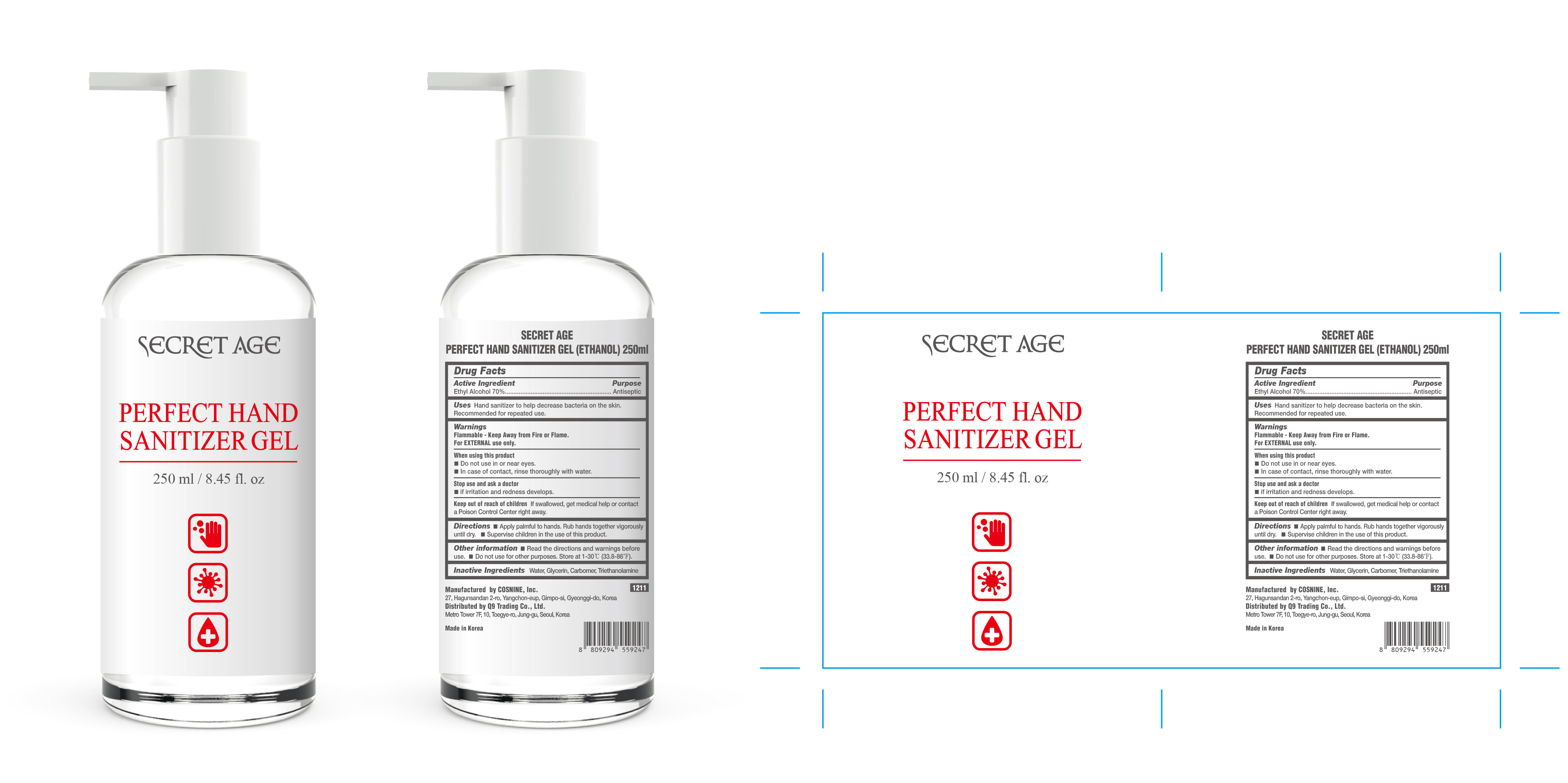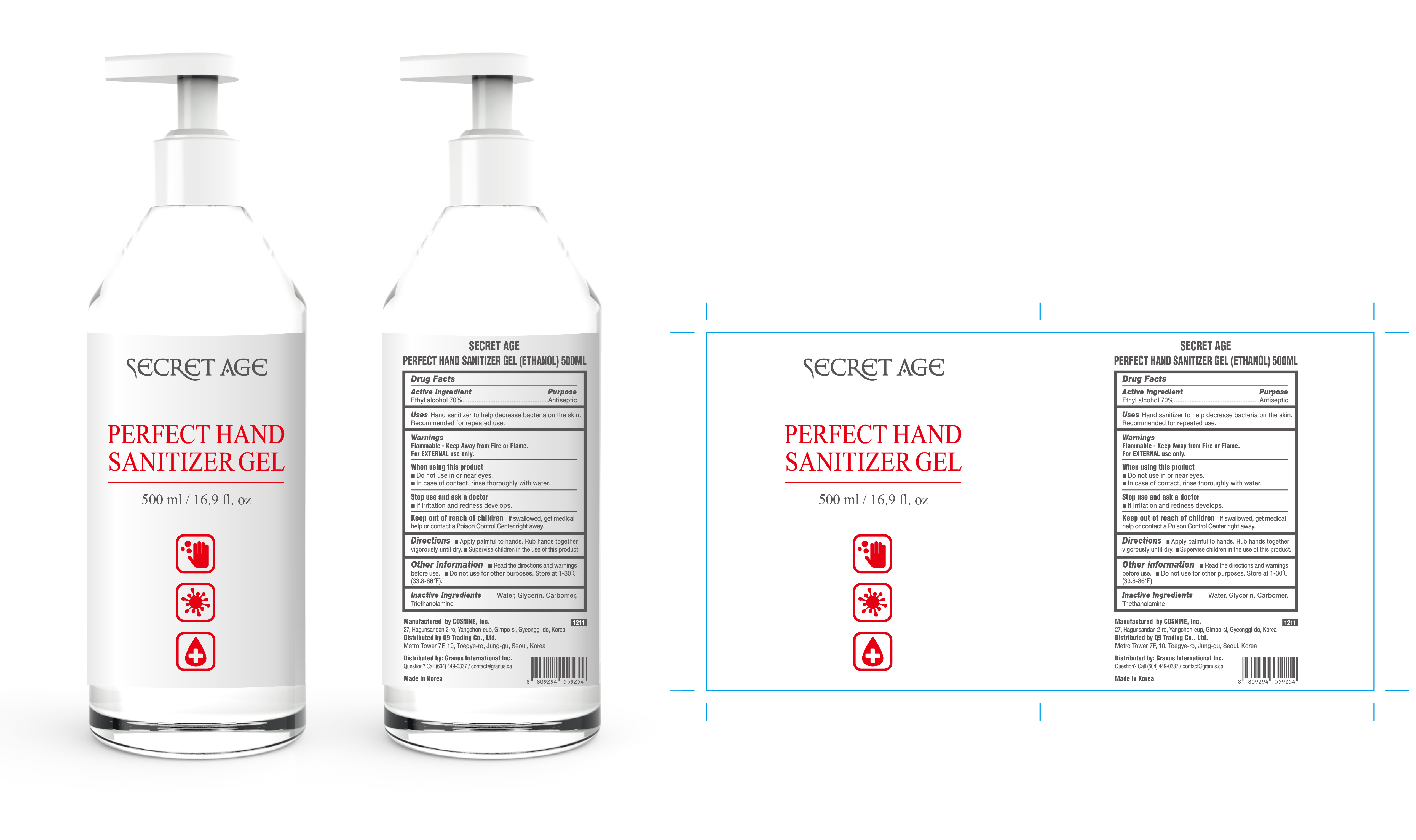 DRUG LABEL: SECRET AGE PERFECT HAND SANITIZER (ETHANOL)
NDC: 73330-0011 | Form: GEL
Manufacturer: COSNINE Inc
Category: otc | Type: HUMAN OTC DRUG LABEL
Date: 20200517

ACTIVE INGREDIENTS: ALCOHOL 0.7 mL/1 mL
INACTIVE INGREDIENTS: GLYCERIN; CARBOMER HOMOPOLYMER TYPE C (ALLYL PENTAERYTHRITOL CROSSLINKED); WATER; TROLAMINE

Active Ingredient(s)

Ethyl Alcohol 70%

Purpose

Antiseptic

Uses

Hand sanitizer to help decrease bacteria on the skin.

Recommended for repeated use.

Warnings

Flammable - Keep away from fire or flame

For EXTERNAL use only.

When using this product

- Do not use in or near eyes.
- In case of contact, rinse thoroughly with water.

Stop use and ask a doctor

if irritation and redness develops.

Keep out of reach of children

if swallowed, get medical help or contact a Poison Control Center right away.

Directions

- Apply palmful to hands. Rub hands together vigorously until dry.
- Supervise children in the use of this product.

Other information

- Read the directions and warnings before use.
- Do not use for other purposes.
- Store at 1-30oC (33.8-86oF).

Inactive ingredients

Water, Glycerin, Carbomer, Triethanolamine

Package Label - Principal Display Panel

500 mL NDC: 73330-0011-1

250 mL NDC: 73330-0011-2

100 mL NDC: 73330-0011-3